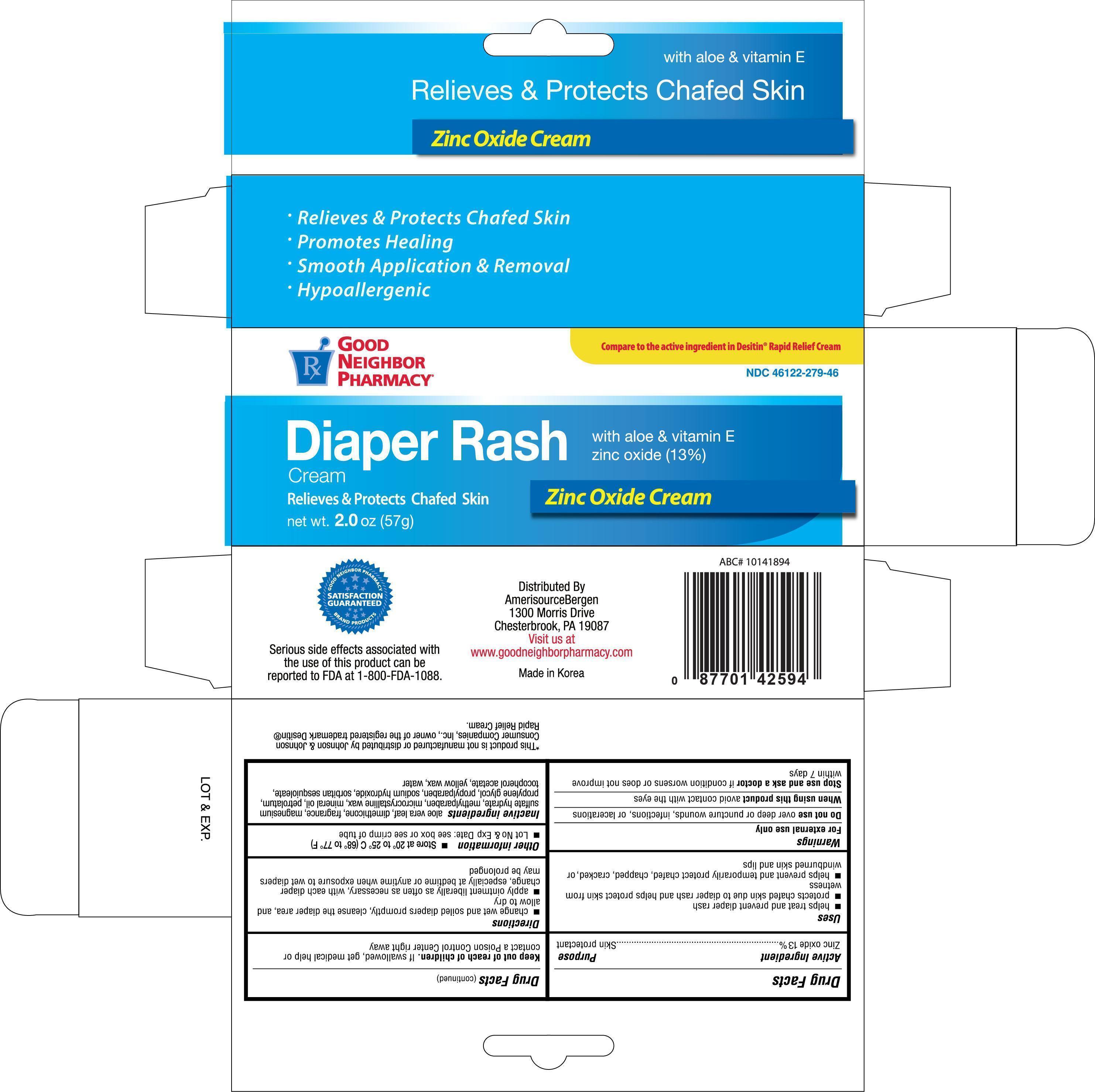 DRUG LABEL: Good Neighbor Pharmacy Diaper Rash
NDC: 46122-279 | Form: CREAM
Manufacturer: Amerisource Bergen
Category: otc | Type: HUMAN OTC DRUG LABEL
Date: 20161006

ACTIVE INGREDIENTS: ZINC OXIDE 13 mg/1 g
INACTIVE INGREDIENTS: ALOE VERA LEAF; DIMETHICONE; METHYLPARABEN; MICROCRYSTALLINE WAX; MINERAL OIL; PETROLATUM; PROPYLENE GLYCOL; PROPYLPARABEN; SODIUM HYDROXIDE; SORBITAN SESQUIOLEATE; ALPHA-TOCOPHEROL ACETATE; YELLOW WAX; WATER

Active Ingredient Purpose

Zinc oxide 13%.................................................. Skin protectant

Uses

- helps treat and prevent diaper rash
- protects chafed skin due to diaper rash and helps protect skin from wetness
- helps prevent and temporarily protect chafed, chapped, cracked, or windburned skin and lips

Warnings

For external use only

Do not use over deep or puncture wounds, infections, or lacerations

When using this product avoid contact with the eyes

Stop use and ask a doctor if condition worsens or does not improve within 7 days

Keep out of reach of children. If swallowed, get medical help or contact a Poison Control Center right away

Directions

- change wet and soiled diapers promptly, cleanse the diaper area, and allow to dry
- apply ointment liberally as often as necessary, with each diaper change, especialy at bedtime or anything when exposure to wet diapers may be prolonged

Other information

- Store at 20° to 25°C (68° to 77° F)
- Lot No & Exp Date: see box or see crimp of tube

INACTIVE INGREDIENT

Inactive ingredients aloe vera leaf, dimethicone, fragrance, magnesium sulfate hydrate, methylparaben, microcrystalline wax, mineral oil, petrolatum, propylene glycol, propylparaben, sodium hydroxide, sorbitan sesquioleate, tocopherol acetate, yellow wax, water

DOSAGE AND ADMINISTRATION

DISTRIBUTED BY:

Amerisource Bergen

1300 Morris Drive

Chesterbrook, PA 19087

Made in Korea